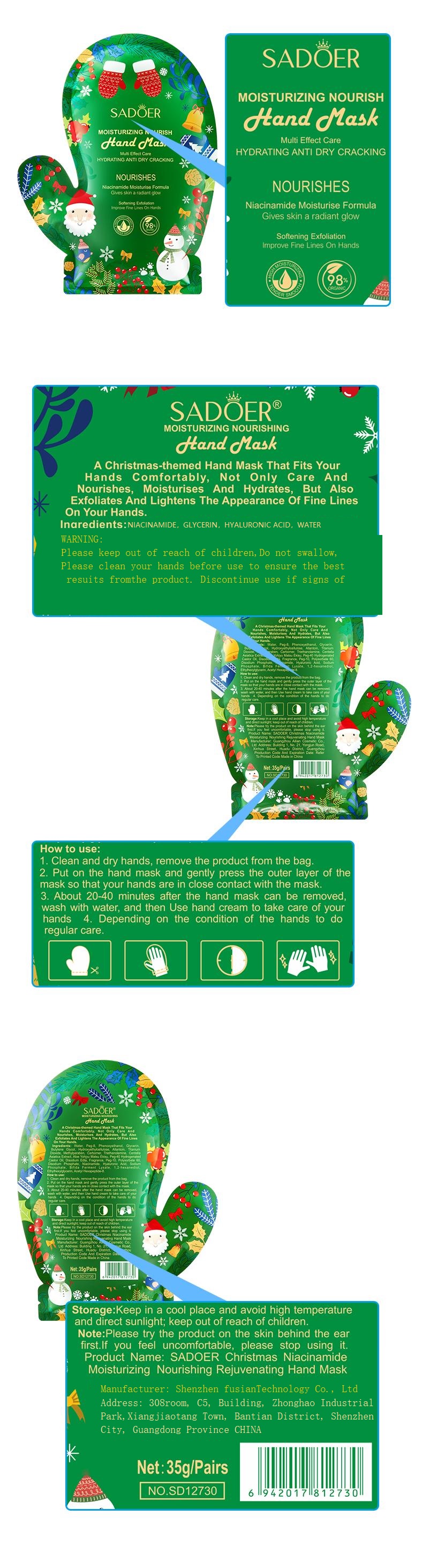 DRUG LABEL: SODOER HAND MASK
NDC: 84775-043 | Form: CREAM
Manufacturer: Shenzhen Fusian Technology Co Ltd
Category: otc | Type: HUMAN OTC DRUG LABEL
Date: 20241122

ACTIVE INGREDIENTS: GLYCERIN 11 g/35 g; HYALURONIC ACID 2 g/35 g; WATER 20 g/35 g
INACTIVE INGREDIENTS: NIACINAMIDE 2 g/35 g

ACTIVE INGREDIENT

NIACINAMIDE 5.7%

GLYCERIN 31.4%

HYALURONIC ACID 5.7%

WATER 57.1%

PURPOSE

Niacinamide Moisturise FormulaGives skin a radiant glow
Softening ExfoliationImprove Fine Lines On Feet

INDICATIONS AND USAGE

How to use:
1.Clean and dry your feet, then remove the productfrom the bag.

2.Put on the foot mask, gently press the outer layer ofthe mask so that the foot is in close contact with themask.

3.After about 20-40 minutes, you can take off the footmask, wash with water, and then use foot cream totake care of your feet.

4.Depending on the condition of the feet to do regularcare.

WARNINGS

For exdamal use only

Stop use and ask a doctor if

rash occurs

Do not use

on damagod or broken skn

Keep out of reach of chiidren!

If swallowed, get medical help or contact a Poison Control Center right away

When using this product

keep out of eyes. Rinse with water to remove

Directions

Dosage recommendations:
Use one pair of hand masks each time (one for each hand).
Use frequency:
Moisturizing foot mask: 1-2 times a week.
Exfoliating foot mask: 1-2 times a month, depending on personal needs and product instructions

INACTIVE INGREDIENT

Peg-8, Phenoxyethanol.